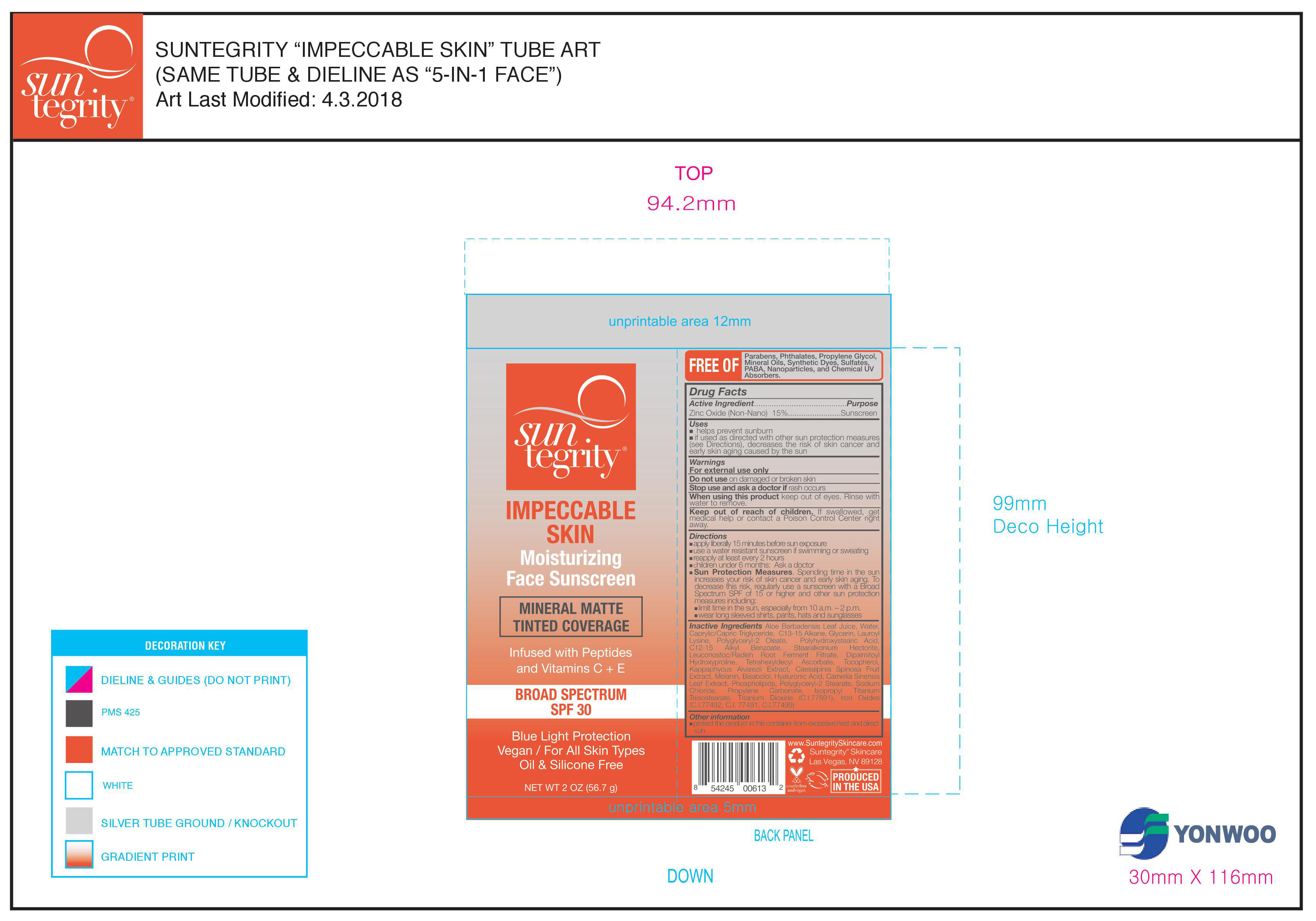 DRUG LABEL: Impeccable Skin Moisturizing Face Sunscreen Broad Spectrum SPF 30
NDC: 56152-0100 | Form: CREAM
Manufacturer: Cosmetic Enterprises LTD
Category: otc | Type: HUMAN OTC DRUG LABEL
Date: 20251010

ACTIVE INGREDIENTS: ZINC OXIDE 15 g/100 g
INACTIVE INGREDIENTS: EGG PHOSPHOLIPIDS; SODIUM CHLORIDE; C13-15 ALKANE; LAUROYL LYSINE; POLYGLYCERYL-2 STEARATE; HYALURONIC ACID; FERRIC OXIDE YELLOW; KAPPAPHYCUS ALVAREZII; LEVOMENOL; GREEN TEA LEAF; POLYGLYCERYL-2 OLEATE; POLYHYDROXYSTEARIC ACID (2300 MW); STEARALKONIUM HECTORITE; PROPYLENE CARBONATE; FERRIC OXIDE RED; TITANIUM DIOXIDE; FERROSOFERRIC OXIDE; MEDIUM-CHAIN TRIGLYCERIDES; LEUCONOSTOC/RADISH ROOT FERMENT FILTRATE; WATER; DIPALMITOYL HYDROXYPROLINE; TOCOPHEROL; TETRAHEXYLDECYL ASCORBATE; ALKYL (C12-15) BENZOATE; MELANIN SYNTHETIC (TYROSINE, PEROXIDE); ALOE VERA LEAF; GLYCERIN

Impeccable Skin Moisturizing Face Sunscreen Broad Spectrum SPF 30

Active ingredient ............................Purpose

Zinc Oxide (non- nano) 15%........Sunscreen

Uses

- Helps Prevent Sunburn
- If used as directed with other sun protection measures (see Directions), decreases the risk of skin cancer and early skin aging caused by the sun.

Keep out of reach of children.If product is swallowed, get medical help or contact a poison Control Center right away.

Stop use and ask a doctor ifrash occurs

Warnings

For external use only
Do not useon damaged or broken skin
When using this productkeep out of eyes. Rinse with water to remove

Directions

- apply liberally 15 minutes before sun exposure
- use a water-resistant sunscreen if swimming or sweating
- reapply at least every 2 hours.
- children under 6 months of age: ask a doctor.
- Sun Protection MeasuresSpending time in the sun increases your risk of skin cancer and early skin aging. To decrease this risk, regularly use a sunscreen with a Broad-Spectrum SPF value of 15 or higher and other sun protection measures including:
- limit your time in the sun, especially from 10 a.m. – 2 p.m.
- wear long-sleeved shirts, pants, hats, and sunglasses

INACTIVE INGREDIENT

Inactive ingredientsAloe Barbadensis Leaf Juice, Water, Caprylic/Capric Triglyceride, C13-15 Alkane, Glycerin, Lauroyl Lysine, Polyglyceryl-2 Oleate, Polyhydroxystearic Acid, C12-15 Alkyl Benzoate, Stearalkonium Hectorite, Leuconostoc/Radish Root Ferment Filtrate, Dipalmitoyl Hydroxyproline, Tetrahexyldecyl Ascorbate, Tocopherol, Kappaphycus Alvarezii Extract, Caesalpina Spinosa Fruit Extract, Melanin, Bisabolol, Hyaluronic Acid, Camellia Sinensis Leaf Extract, Phospholipids, Polyglyceryl-2 Stearate, Sodium Chloride, Propylene Carbonate, Isopropyl Titanium Trisostearate, Titanium Dioxide (C.I. 77891), Iron Oxides (C.I.77492, C.I. 77491, C.I. 77499)

PACKAGE LABEL

Suntegrity

Impeccable skin

Moisturizing Face Sunscreen

Mineral AMtte Tinted Coverage

Infused with peptides and Vitamins C + E

Broad Spectrum SPF 30

Blue Light Protection

Vegan / For all skin types

Oil & Silicon Free

Net Wt. 2 OZ (56.7 g)